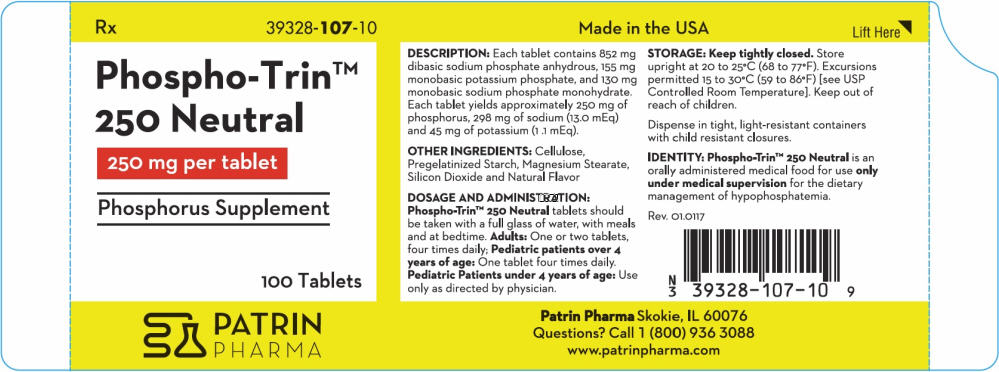 DRUG LABEL: Phospho-Trin 250 Neutral
NDC: 39328-107 | Form: TABLET
Manufacturer: Patrin Pharma, Inc.
Category: other | Type: MEDICAL FOOD
Date: 20170209

ACTIVE INGREDIENTS: SODIUM PHOSPHATE, DIBASIC, ANHYDROUS 852 mg/1 1; POTASSIUM PHOSPHATE, MONOBASIC 155 mg/1 1; SODIUM PHOSPHATE, MONOBASIC, MONOHYDRATE 130 mg/1 1
INACTIVE INGREDIENTS: Microcrystalline Cellulose; Starch, Corn; Magnesium Stearate; Silicon Dioxide

Phospho-Trin™ 250 Neutral
Phosphorus Supplement
250 mg per tablet

DESCRIPTION

Each tablet contains 852 mg dibasic sodium phosphate anhydrous, 155 mg monobasic potassium phosphate, and 130 mg monobasic sodium phosphate monohydrate. Each tablet yields approximately 250 mg of phosphorus, 298 mg of sodium (13.0 mEq) and 45 mg of potassium (1 .1 mEq).

OTHER INGREDIENTS

Cellulose, Pregelatinized Starch, Magnesium Stearate, Silicon Dioxide and Natural Flavor

CLINICAL PHARMACOLOGY

Phosphorus has a number of important functions in the biochemistry of the body. The bulk of the body's phosphorus is located in the bones, where it plays a key role in osteoblastic and osteoclastic activities. Enzymatically catalyzed phosphate-transfer reactions are numerous and vital in the metabolism of carbohydrate, lipid and protein, and a proper concentration of the anion is of primary importance in assuring an orderly biochemical sequence. ln addition, phosphorus plays an important role in modifying steady-state tissue concentrations of calcium. Phosphate ions are important buffers of the intracellular fluid, and also play a primary role in the renal excretion of the hydrogen ion.

Oral administration of inorganic phosphates increases serum phosphate levels. Phosphates lower urinary calcium levels in idiopathic hypercalciuria.

In general, in adults, about two thirds of the ingested phosphate in absorbed from the bowel, most of which is rapidly excreted into the urine.

INDICATIONS AND USAGE

Phospho-Trin™ 250 Neutral increases urinary phosphate and pyrophosphate. As a phosphorus supplement, each tablet supplies 25% of the U.S. Recommended Daily Allowance (U.S. RDA) of phosphorus for adults and children over 4 years of age.

CONTRAINDICATIONS

This product is contraindicated in patients with infected phosphate stones, in patients with severely impaired renal function (less than 30% of normal) and in the presence of hyperphosphatemia.

PRECAUTIONS

General

This product contains potassium and sodium and should be used with caution if regulation of these elements is desired. Occasionally, some individuals may experience a mild laxative effect during the first few days of phosphate therapy. If laxation persists to an unpleasant degree reduce the daily dose until this effect subsides or, if necessary, discontinue the use of the product.

Caution should be exercised when prescribing this product in the following conditions: Cardiac disease (particularly in digitalized patients); severe adrenal insufficiency (Addison's disease); acute dehydration; severe renal insufficiency; renal function impairment or chronic renal disease; extensive tissue breakdown (such as severe burns); myotonia congenita; cardiac failure; cirrhosis of the liver or severe hepatic disease; peripheral or pulmonary edema; hypernatremia; hypertension; toxemia of pregnancy; hypoparathyroidism; and acute pancreatitis. Rickets may benefit from phosphate therapy, but caution should be exercised. High serum phosphate levels may increase the incidence of extraskeletal calcification.

Information for Patients

Patients with kidney stones may pass old stones when phosphate therapy is started and should be warned of this possibility. Patients should be advised to avoid the use of antacids containing aluminum, magnesium, or calcium which may prevent the absorption of phosphate.

Laboratory

Careful monitoring of renal function and serum calcium, phosphorus, potassium, and sodium may be required at periodic intervals during phosphate therapy. Other tests may be warranted in some patients, depending on conditions.

Drug Interactions

The use of antacids containing magnesium, aluminum, or calcium in conjunction with phosphate preparations may bind the phosphate and prevent its absorption. Concurrent use of antihypertensives, especially diazoxide, guanethidine, hydralazine, methyldopa, or rauwolfia alkaloid; or corticosteroids, especially mineralocorticoids or corticotropin with sodium phosphate may result in hypernatremia. Calcium-containing preparations and/or Vitamin D may antagonize the effects of phosphates in the treatment of hypercalcemia. Potassium-containing medication or potassium-sparing diuretics may cause hyperkalemia. Patients should have serum potassium level determinations at periodic intervals.

Carcinogenesis, Mutagenesis, Impairment of Fertility

No long term or reproduction studies in animals or humans have been performed with Phospho-Trin™ 250 Neutral to evaluate its carcinogenic, mutagenic, or impairment of fertility potential.

Pregnancy

Teratogenic Effects

Pregnancy Class C

Animal reproduction studies have not been conducted with Phospho-Trin™ 250 Neutral. It is also not known whether this product can cause fetal harm when administered to a pregnant woman or can affect reproductive capacity.

This product should be given to a pregnant woman only if clearly needed.

Nursing Mothers

It is not known whether this drug is excreted in human milk. Because many drugs are excreted in human milk, caution should be exercised when this product is administered to a nursing woman.

Pediatric Use

See DOSAGE AND ADMINISTRATION.

ADVERSE REACTIONS

Gastrointestinal upset (diarrhea, nausea, stomach pain, and vomiting) may occur with phosphate therapy. Also, bone and joint pain (possible phosphate-induced osteomalacia) could occur. The following adverse effects may be observed (primarily from sodium or potassium): headaches; dizziness; mental confusion; seizures; weakness or heaviness of legs; unusual tiredness or weakness; muscle cramps; numbness, tingling, pain or weakness of hands or feet; numbness or tingling around lips; fast or irregular heartbeat; shortness of breath or troubled breathing; swelling of feet or lower legs; unusual weight gain; low urine output; unusual thirst.

DOSAGE AND ADMINISTRATION

Phospho-Trin™ 250 Neutral tablets should be taken with a full glass of water, with meals and at bedtime.

Adults

One or two tablets, four times daily;

Pediatric patients over 4 years of age

One tablet four times daily.

Pediatric Patients under 4 years of age

Use only as directed by physician.

HOW SUPPLIED

White, oval-shaped tablet, debossed with P107 on each tablet.

NDC #39328-107-10
Bottles of 100 tablets

STORAGE

Keep tightly closed. Store upright at 20 to 25°C (68 to 77°F). Excursions permitted 15 to 30°C (59 to 86°F) [see USP Controlled Room Temperature]. Keep out of reach of children. Dispense in tight, light-resistant containers with child resistant closures.

IDENTITY

Phospho-Trin™ 250 Neutral is an orally administered medical food for use only under medical supervision for the dietary management of hypophosphatemia.

Manufactured for:
Patrin Pharma, Inc.
P.O. Box 1481
Skokie, IL 60076

PRINCIPAL DISPLAY PANEL - 100 Tablet Bottle Label

Rx
39328-107-10

Phospho-Trin™
250 Neutral

250 mg per tablet

Phosphorus Supplement

100 Tablets

PATRIN
PHARMA